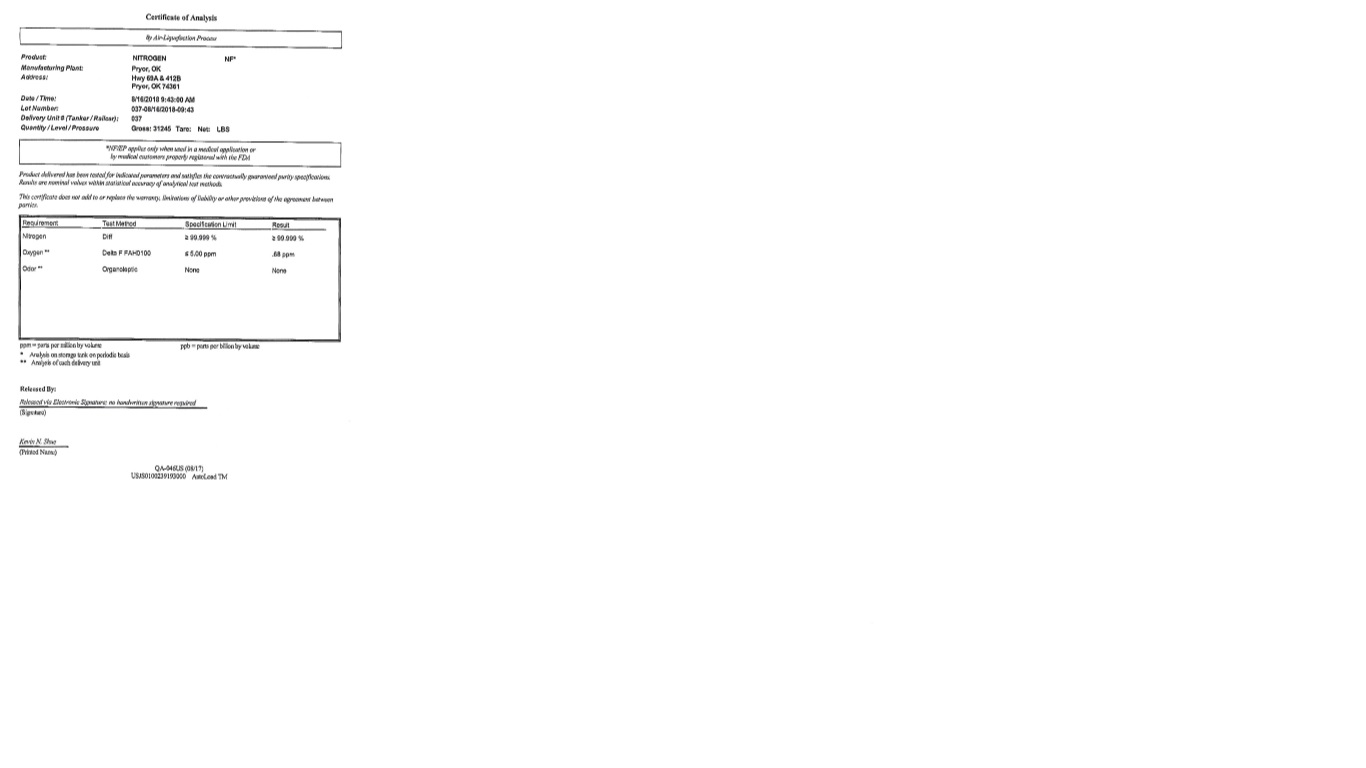 DRUG LABEL: Nitrogen
NDC: 42751-1073 | Form: GAS
Manufacturer: FULLERTON WELDING SUPPLY
Category: prescription | Type: HUMAN PRESCRIPTION DRUG LABEL
Date: 20251121

ACTIVE INGREDIENTS: NITROGEN 990 mL/1 L

Nitrogen

PACKAGE LABEL

Certificate of Analysis

By Air-Liquefaction Process

Product: NITROGEN NF*

Manufacturing Plant: Pryor, OK

Address: Hwy 69A & 412 B

Pryor, OK 74361

Date / Time: 8/16/2018 9:43:00 AM

Lot Number: 037-08/16/2018/09:43

Delivery Unit # (Tanker / Railcar): 037

Quantity / Level / Prossure Gross: 31245 Tare: Net: LBS

*NF/EP applies only when used in a medical application or by medical customers properly registered with the FDA

Product delivered has been tested for indicated parameters and satisfies the contractually guaranteed purity specifications. Results are nominal values within statistical accuracy of analytical test methods.

This certificate does not add to or replace the warranty, limitations of liablilty or other provisions of the agreement between parties.

Requirement Test Method Specification Limit Result

Nitrogen Diff ≥ 99.999 percent ≥ 99.999 percent

Oxygen ** Delta F FAH0100 ≤ 5.00 ppm .68 ppm

Odor ** Organoleptic None None

Ppm = parts per million by volume ppb = parts per billion by volume

*Analysis on storage tank on periodic basis

**Analysis of each delivery unit

Released By:

Released via Electronic Signature: no handwritten signature required

(Signature)

Kevin N. Shue

(Printed Name)

QA-046US (08/17)

USJS0I00239193000 AutoLand TM